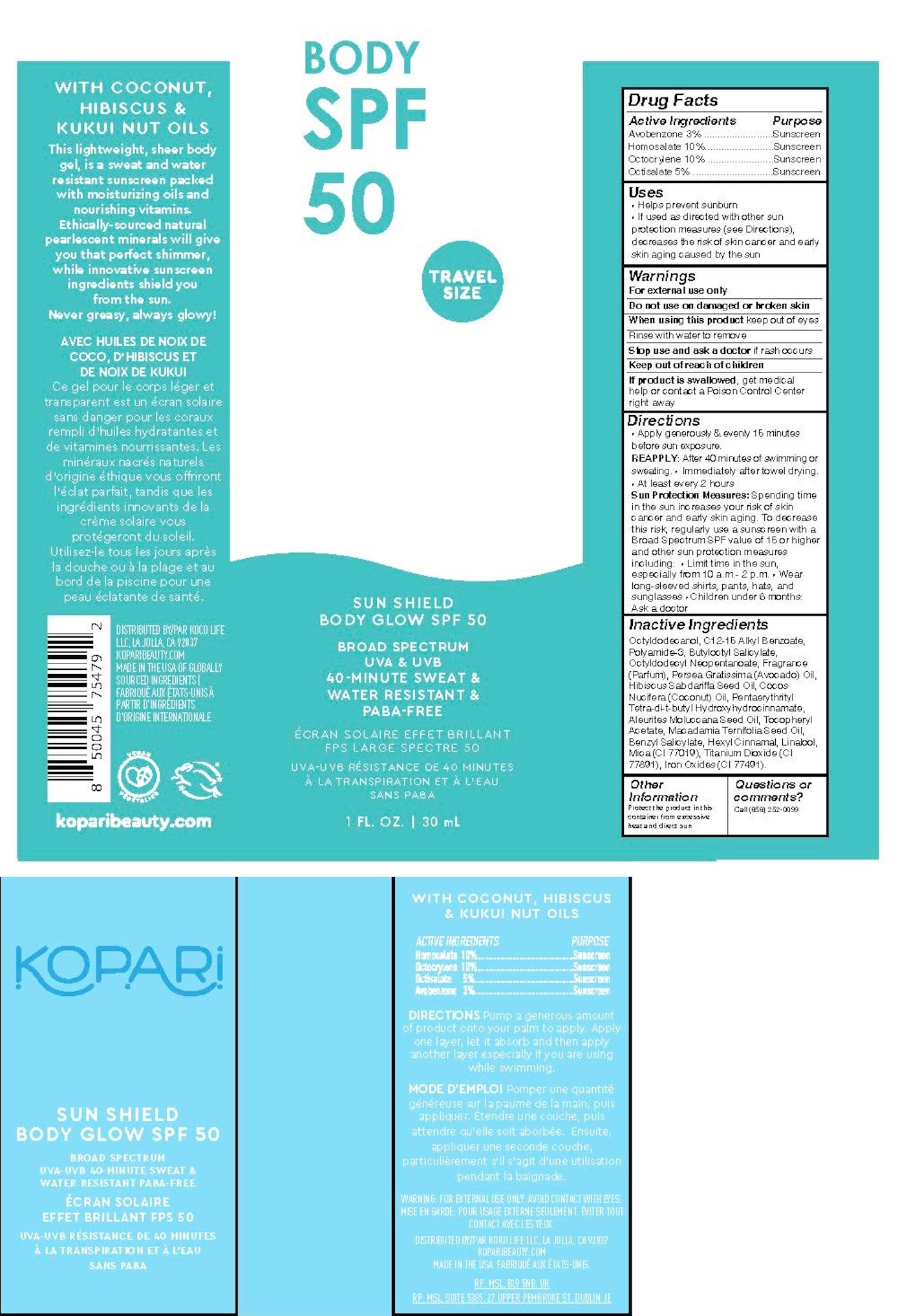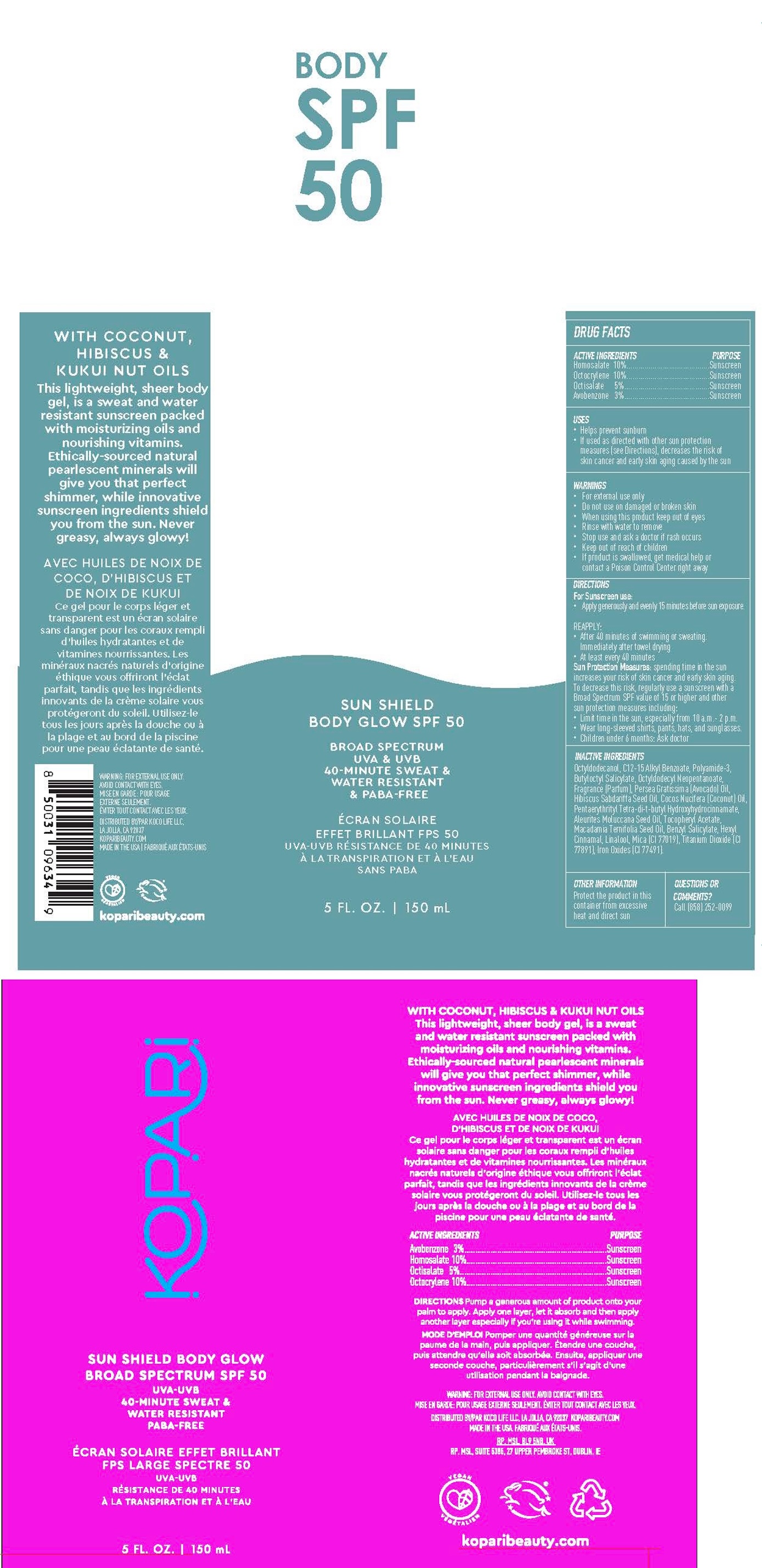 DRUG LABEL: Sun Shield Body Glow SPF50
NDC: 84130-001 | Form: GEL
Manufacturer: Koco Life LLC
Category: otc | Type: HUMAN OTC DRUG LABEL
Date: 20240628

ACTIVE INGREDIENTS: OCTOCRYLENE 100 mg/1 mL; HOMOSALATE 100 mg/1 mL; AVOBENZONE 30 mg/1 mL; OCTISALATE 50 mg/1 mL
INACTIVE INGREDIENTS: POLYAMIDE-3 (12000 MW); BUTYLOCTYL SALICYLATE; PENTAERYTHRITOL TETRAKIS(3-(3,5-DI-TERT-BUTYL-4-HYDROXYPHENYL)PROPIONATE); TITANIUM DIOXIDE; .ALPHA.-TOCOPHEROL ACETATE; FERRIC OXIDE RED; BENZYL SALICYLATE; LINALOOL, (+/-)-; AVOCADO OIL; MACADAMIA OIL; OCTYLDODECANOL; MICA; OCTYLDODECYL NEOPENTANOATE; HIBISCUS SABDARIFFA SEED OIL; KUKUI NUT OIL; ALKYL (C12-15) BENZOATE; .ALPHA.-HEXYLCINNAMALDEHYDE; COCONUT OIL

Sun Shield Body Glow SPF50
Sun Shield Body Glow SPF50 DX

Active Ingredients

Homosalate 10%

Octocrylene 10%

Octisalate 5%

Avobenzone 3%

Purpose

Homosalate 10%.........................................Sunscreen

Octocrylene 10%.........................................Sunscreen

Octisalate 5%..............................................Sunscreen

Avobenzone 3%..........................................Sunscreen

Uses

• Helps prevent sunburn

• If used as directed with other sun protectionmeasures (see Directions), decreases the risk ofskin cancer and early skin aging caused by the sun

Warnings

• For external use only

• Do not use on damaged or broken skin

• When using this product keep out of eyes

• Rinse with water to remove

• Stop use and ask a doctor if rash occurs

• Keep out of reach of children

• If product is swallowed, get medical help orcontact a Poison Control Center right away

Directions

For Sunscreen use:

• Apply generously and evenly 15 minutes before sun exposure.

REAPPLY:

• After 40 minutes of swimming or sweating.Immediately after towel drying

• At least every 40 minutes

Sun Protection Measures: spending time in the sun increases your risk of skin cancer and early skin aging. To decrease this risk, regularly use a sunscreen with a Broad Spectrum SPF value of 15 or higher and other sun protection measures including:

• Limit time in the sun, especially from 10 a.m.- 2 p.m.

• Wear long-sleeved shirts, pants, hats, and sunglasses.

• Children under 6 months: Ask doctor

Inactive ingredients

Octyldodecanol, C12-15 Alkyl Benzoate, Polyamide-3, Butyloctyl Salicylate, Octyldodecyl Neopentanoate, Fragrance (Parfum), Persea Gratissima (Avocado) Oil, Hibiscus Sabdariffa Seed Oil, Cocos Nucifera (Coconut) Oil, Pentaerythrityl Tetra-di-t-butyl Hydroxyhydrocinnamate, Aleurites Moluccana Seed Oil, Tocopheryl Acetate, Macadamia Ternifolia Seed Oil, Benzyl Salicylate, Hexyl Cinnamal, Linalool, Mica (CI 77019), Titanium Dioxide (CI 77891), Iron Oxides (CI 77491).

Other information

Protect the product in this container from excessive heat and direct sun

Questions or Comments?

Call (858) 252-0099

PACKAGE LABEL

Sun Shield Body Glow SPF 50

Broad Spectrum

UVA & UVB

40-Minute Sweat &

Water Resistant

& PABA-Free